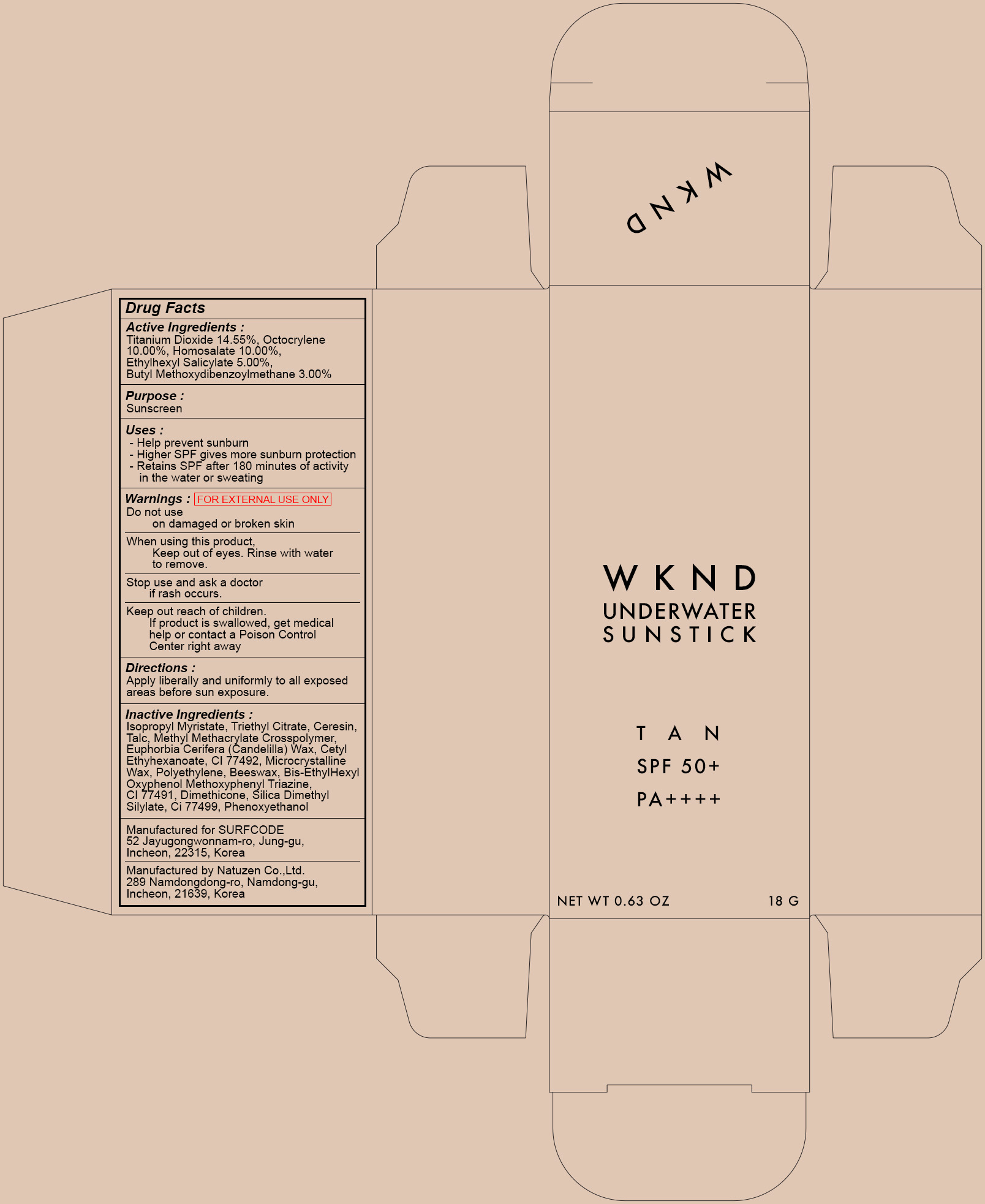 DRUG LABEL: WKND UNDERWATER SUN TAN
NDC: 71192-040 | Form: STICK
Manufacturer: SURFCODE
Category: otc | Type: HUMAN OTC DRUG LABEL
Date: 20191223

ACTIVE INGREDIENTS: Titanium Dioxide 2.61 g/18 g; Octocrylene 1.80 g/18 g; Homosalate 1.80 g/18 g; Octisalate 0.90 g/18 g; Avobenzone 0.54 g/18 g
INACTIVE INGREDIENTS: Isopropyl Myristate; Ceresin

ACTIVE INGREDIENT

Active ingredients: Titanium Dioxide 14.55%, Octocrylene 10.00%, Homosalate 10.00%, Ethylhexyl Salicylate 5.00%, Butyl Methoxydibenzoylmethane 3.00%

INACTIVE INGREDIENT

Inactive Ingredients:

Isopropyl Myristate, Triethyl Citrate , Ceresin, Talc, Methyl Methacrylate Crosspolymer, Euphorbia Cerifera (Candelilla) Wax, Cetyl Ethyhexanoate, CI 77492, Microcrystalline Wax, Polyethylene, Beeswax, Bis-EthylHexylOxyphenol Methoxyphenyl Triazine, CI 77491, Dimethicone, Silica Dimethyl Silylate , Ci 77499, Phenoxyethanol

PURPOSE

Purpose: Sunscreen

WARNINGS

FOR EXTERNAL USE ONLY

Do not use on damaged or broken skin

When using this product, Keep out of eyes. Rinse with water to remove.

Stop use and ask a doctor if rash occurs.

Keep out reach of children. If product is swallowed, get medical help or contact a Poison Control Center right away

DESCRIPTION

USES:

- Help prevent sunburn

- Higher SPF gives more sunburn protection

- Retains SPF after 180 minutes of activity in the water or sweating

DIRECTION: Apply liberally and uniformly to all exposed areas before sun exposure.